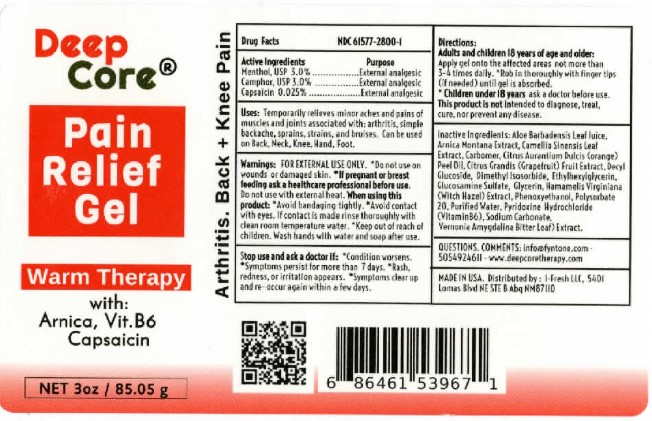 DRUG LABEL: Deep Core Pain Relieving Gel Warm Therapy
NDC: 61577-2800 | Form: GEL
Manufacturer: SOMBRA COSMETICS INC.
Category: otc | Type: HUMAN OTC DRUG LABEL
Date: 20240301

ACTIVE INGREDIENTS: CAMPHOR (SYNTHETIC) .03 g/0.03 g; MENTHOL .03 g/0.03 g
INACTIVE INGREDIENTS: WATER; CARBOMER HOMOPOLYMER TYPE C; ALOE AFRICANA LEAF; GLYCERIN; DECYL GLUCOSIDE; ARNICA MONTANA FLOWER WATER; CAPSAICIN; PYRIDOXINE HYDROCHLORIDE; GRAPEFRUIT SEED OIL; GLUCOSAMINE SULFATE; VERNONIA APPENDICULATA LEAF; ORANGE PEEL; GREEN TEA LEAF; DIMETHYL SULFONE; POLYSORBATE 20; DIMETHYL ISOSORBIDE; PHENOXYETHANOL; ETHYLHEXYLGLYCERIN; SODIUM CARBONATE

Deep Core Pain Relief Gel Warm Therapy

Active Ingredients

Menthol USP 3%, Camphor 3%, Capsaicin 0.025%

Purpose

External Analgesic

Keep out of reach of children

Uses

Temporarily relieves minor aches and pains of muscles and joints associated with: arthritis, simple backaches, arthritis, sprains, strains, and bruises.

Warnings

For external use only. Do not use on wounds, damaged, broken, or irritated skin. Do not bandage tightly or apply heating pads or medicated patch to the area of use. If pregnant or breast feedong, ask a healthcare professional before use. Keep out of reach of children and pets.

Directions

Adults 18 years and above: Apply thin layer to the affected area not more than 3-4 times daily. Massage until cream absorbs into skin. Wash hands with water and soap after application. Adults and children 2 - 18 years of age consult a doctor before use. Children aged under 2, do not use.

Inactive Ingredients

Aloe Barbadensis Leaf Juice, Arnica Montana Extract, Camellia Sinensis Leaf Extract, Carbomer, Citrus Aurantium Dulcis (orange) Peel Oil, Citrus Grandis (Grapefruit) Fruit Extract, Decyl Glucoside, Dimethyl Isosorbide, Ethylhexylglycerin, Glucosamine Sulfate, Glycerin, Methylsulfonylmethane (MSM), Phenoxyethanol, Polysorbate 20, Purified Water, Pyridoxine Hydrochloride (Vitamin B6), Sodium Carbonate, Tocopheryl Acetate, Vernonia Amygdalina (Bitter Leaf) Extract, Witch Hazel Extract.

Questions or Comments

505-492-4611